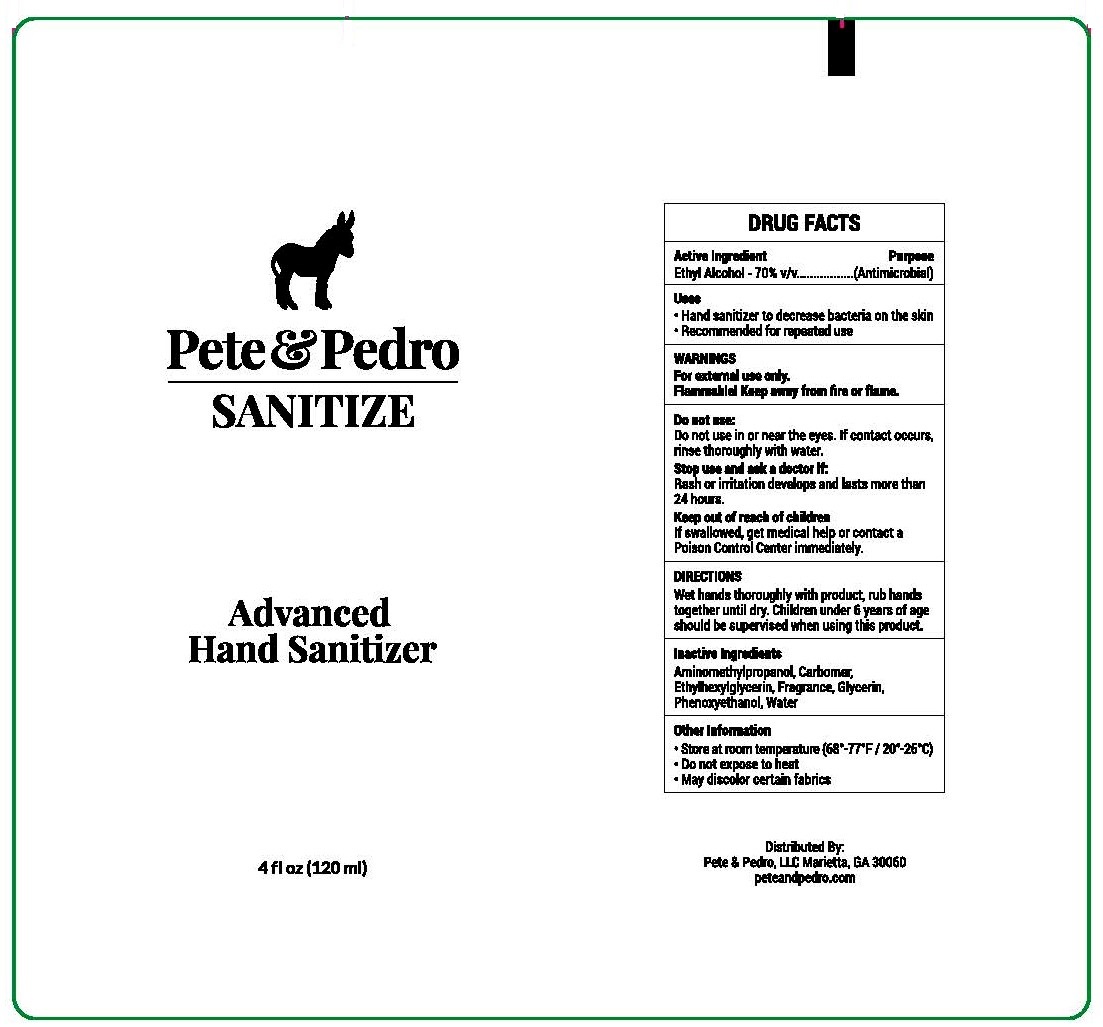 DRUG LABEL: Pete and Pedro Sanitize
NDC: 52261-0901 | Form: GEL
Manufacturer: Cosco International, Inc.
Category: otc | Type: HUMAN OTC DRUG LABEL
Date: 20200501

ACTIVE INGREDIENTS: ALCOHOL 70 L/100 L
INACTIVE INGREDIENTS: GLYCERIN; AMINOMETHYLPROPANOL; CARBOMER HOMOPOLYMER, UNSPECIFIED TYPE; ETHYLHEXYLGLYCERIN; PHENOXYETHANOL; WATER

Active Ingredient(s)

Alcohol 70% v/v. Purpose: Antimicrobial

Purpose

Antimicrobial

Use

- Hand Sanitizer to decrease bacteria on the skin.
- Recommended for repeated use

Warnings

For external use only.

Flammable. Keep away from heat or flame

Do not use in or near the eyes. If contact occurs, rinse throughly with water.

Stop use and ask a doctor if rash or irritation develops and lasts more than 24 hours.

Keep out of reach of children. If swallowed, get medical help or contact a Poison Control Center immediately.

Directions

Wet hands thoroughly with product, rub hands together until dry.
Children under 6 years of age should be supervised when using this product.

Other information

- Store at room temperature (68º-77ºF / 20º-25ºC)
- Do not expose to heat
- May discolor certain fabrics

Inactive Ingredients

Aminomethylpropanol, Carbomer, Ethylhexylglycerin, Fragrance, Glycerin, Phenoxyethanol, Water